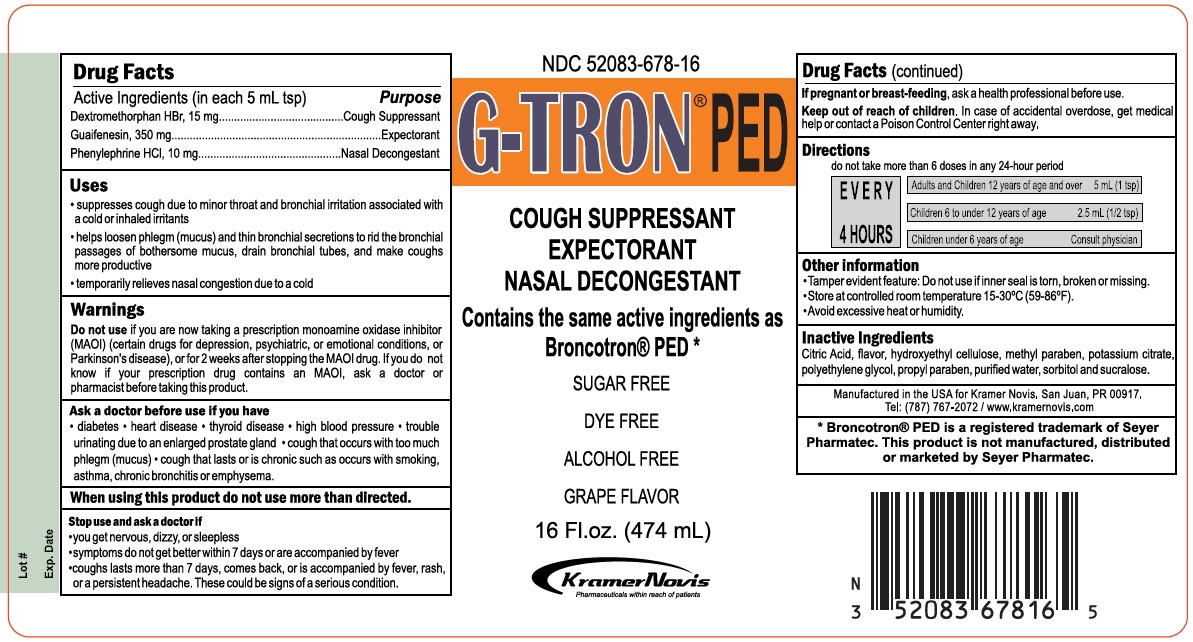 DRUG LABEL: G-TRON
NDC: 52083-678 | Form: SOLUTION
Manufacturer: Kramer Novis
Category: otc | Type: HUMAN OTC DRUG LABEL
Date: 20190916

ACTIVE INGREDIENTS: DEXTROMETHORPHAN HYDROBROMIDE 15 mg/5 mL; GUAIFENESIN 350 mg/5 mL; PHENYLEPHRINE HYDROCHLORIDE 10 mg/5 mL
INACTIVE INGREDIENTS: CITRIC ACID MONOHYDRATE; HYDROXYETHYL CELLULOSE (280 MPA.S AT 5%); METHYLPARABEN; POTASSIUM CITRATE; POLYETHYLENE GLYCOL, UNSPECIFIED; PROPYLPARABEN; WATER; SORBITOL; SUCRALOSE

Drug Facts

Active Ingredients (in each 5 mL tsp) Purpose

Dextromethorphan HBr, 15 mg............................Cough Suppressant

Guaifenesin, 350 mg..............................................Expectorant

Phenylephrine HCl, 10 mg................................Nasal decongestant

Uses

- suppresses cough due to minor throat and bronchial irritation associated with a cold or inhaled irritants
- helps loosen phlegm (mucus) and thin bronchial secretions to rid the bronchial passages of bothersome mucus, drain bronchial tubes, and make coughs more productive
- temporarily relieves nasal congestion due to a cold

Warnings

Do not use if you are now taking a prescription monoamine oxidase inhibitor (MAOI) (certain drugs for depression, psychiatric, or emotional conditions, or Parkinson’s disease), or for 2 weeks after stopping the MAOI drug. If you do not know if your prescription drug contains an MAOI, ask a doctor or pharmacist before taking this product.

Ask a doctor before use if you have

- diabetes
- heart disease
- thyroid disease
- high blood pressure
- trouble urinating due to an enlarged prostate gland
- cough that occurs with too much phlegm (mucus)
- cough that lasts or is chronic such as occurs with smoking, asthma, chronic bronchitis or emphysema.

When using this product do not use more than directed.
Stop use and ask a doctor if

- you get nervous, dizzy or sleepless
- symptoms do not get better within 7 days or are accompanied by fever
- cough last more than 7 days, comes back, or is accompanied by fever, rash or persistent headache. These could be a signs of a serious condition.

PREGNANCY OR BREAST FEEDING

If pregnant or breast-feeding, ask a health professional before use.

Keep out of reach of children. In case of accidental overdose, get medical help or contact a Poison Control Center right away.

Directions

do not take more than 6 doses in any 24-hour period

EVERY 4 HOURS

- Adults and Children 12 years of age and older: 5 mL (1 tsp)
- Children 6 to under 12 years of age: (2.5 mL (1/2 tsp)
- Children under 6 years of age: Consult physician

Other information

Tamper Evident Feature: Do not use if inner seal is torn, broken or missing.

Store at controlled room temperature 15-30°C (59-86°F).

Avoid excessive heat and humidity.

INACTIVE INGREDIENT

Inactive ingredients Citric acid, flavor, hydroxyethyl cellulose, methyl paraben, potassium citrate, polyethylene glycol, propyl paraben, purified water, sorbitol and sucralose.

QUESTIONS

Manufactured in the USA for Kramer-Novis, San Juan, PR 00917.
Tel: (787) 767-2072 / www.kramernovis.com

Principal Display Panel

G-TRON® PED

COUGH SUPPRESSANT

EXPECTORANT

NASAL DECONGESTANT

Contains the same active ingredients as Broncotron® PED

SUGAR FREE

DYE FREE

ALCOHOL FREE

GRAPE FLAVOR

16 Fl. Oz. (474 mL)

KRAMER-NOVIS